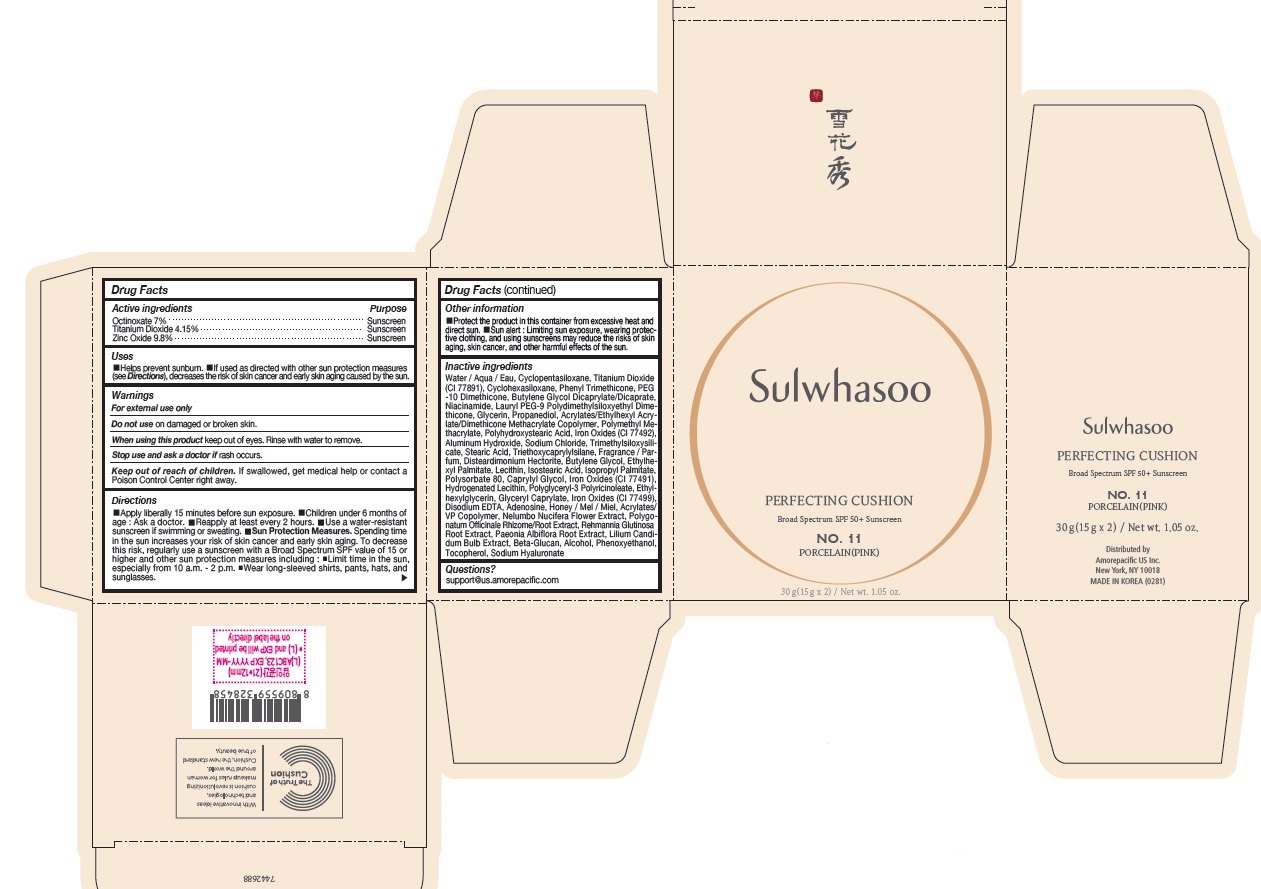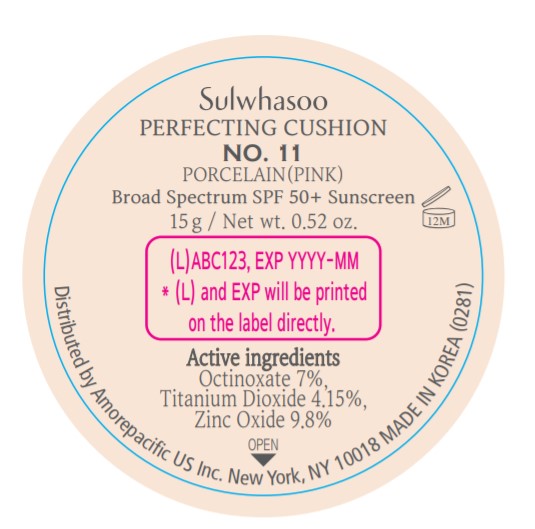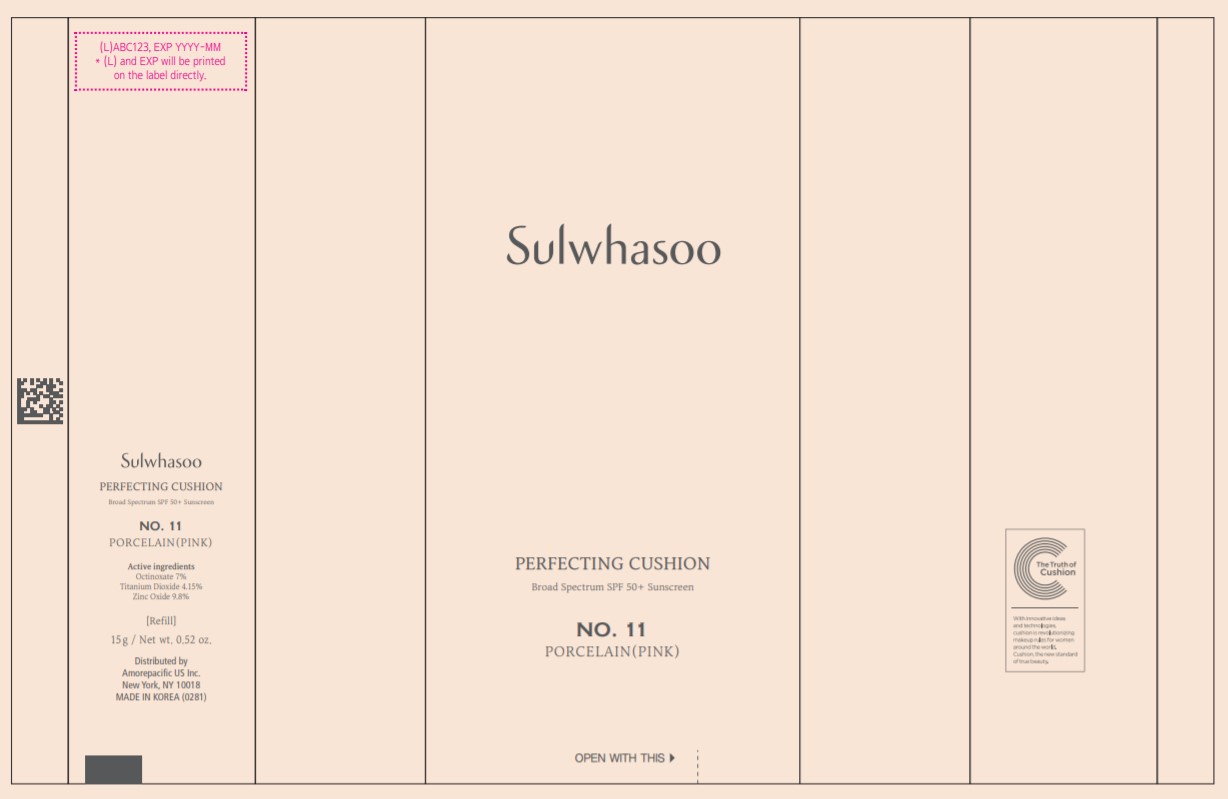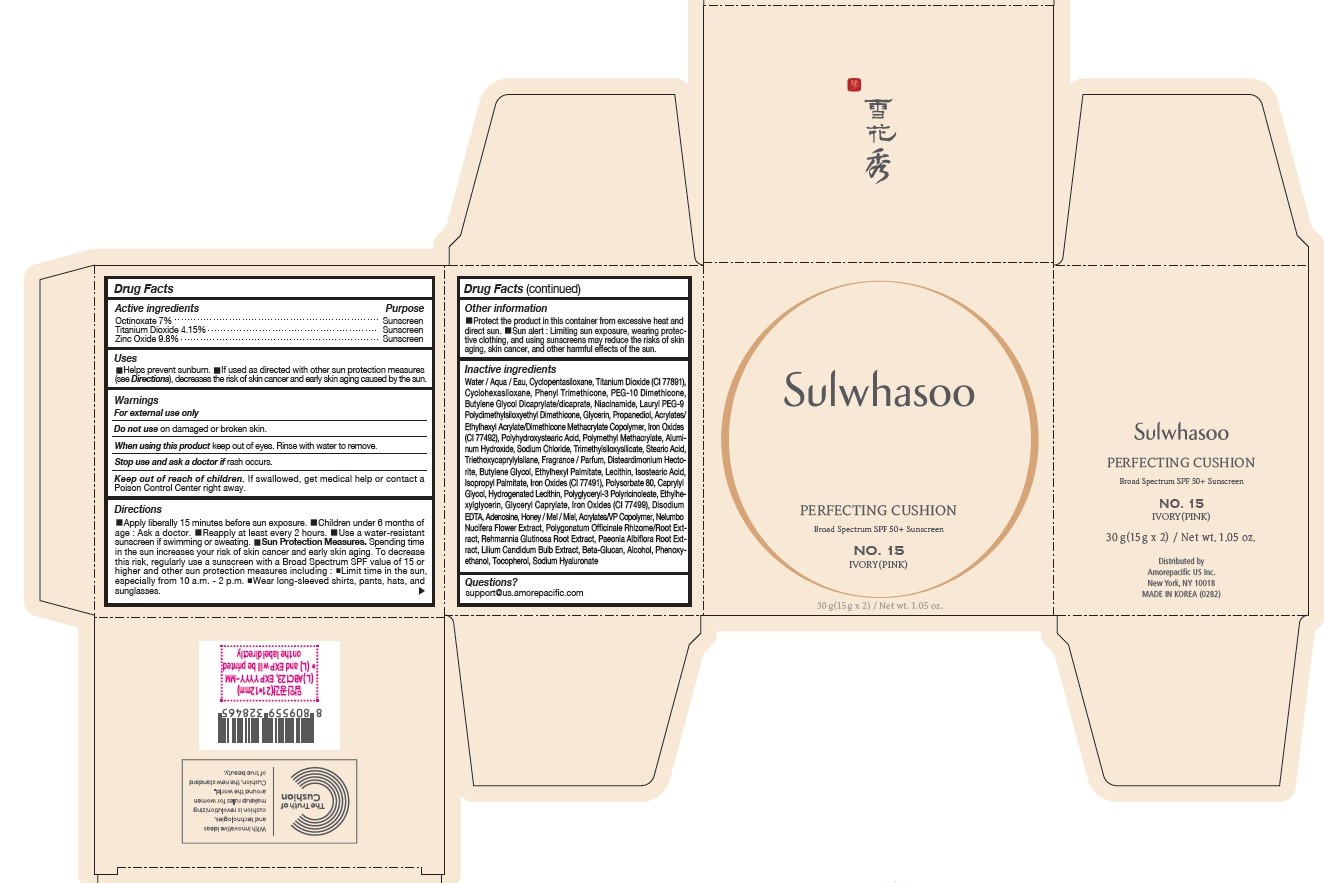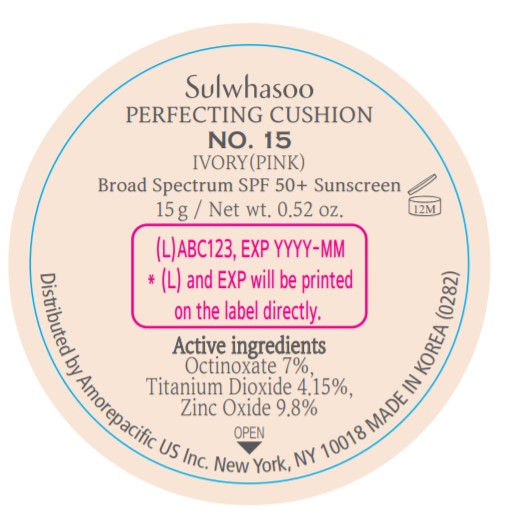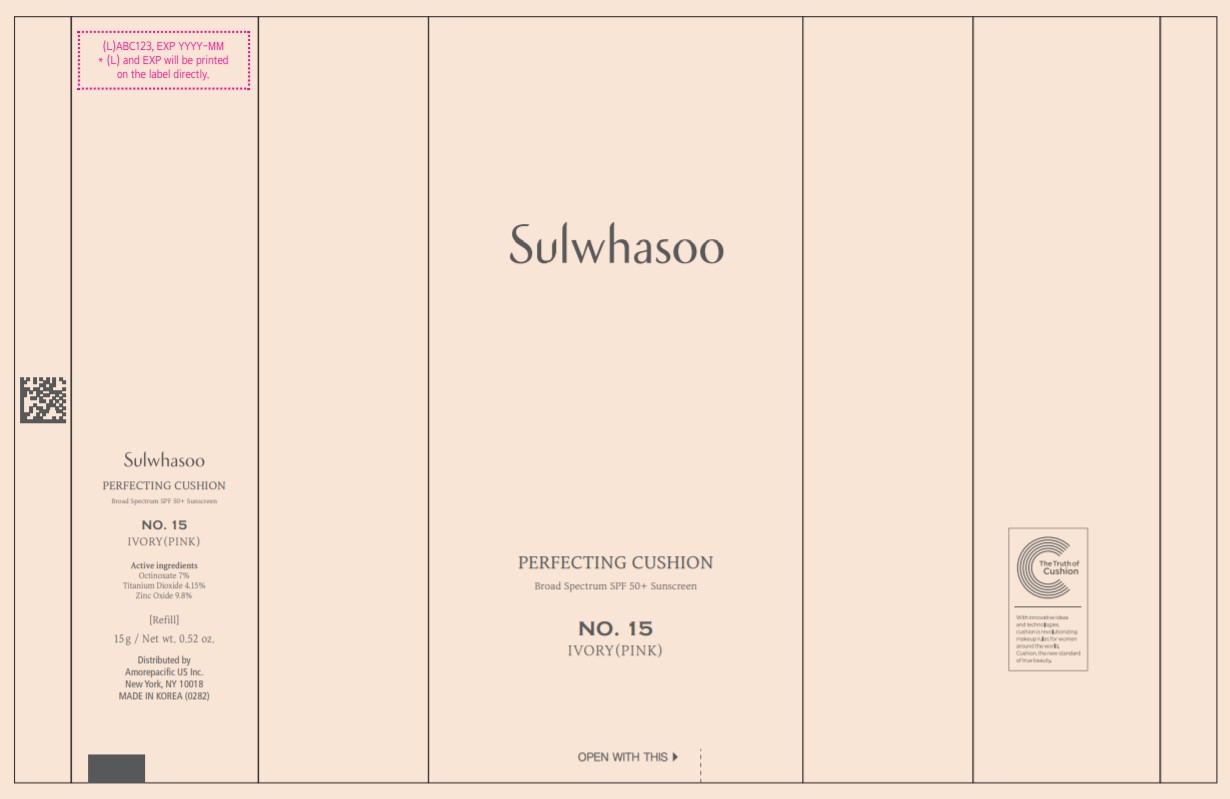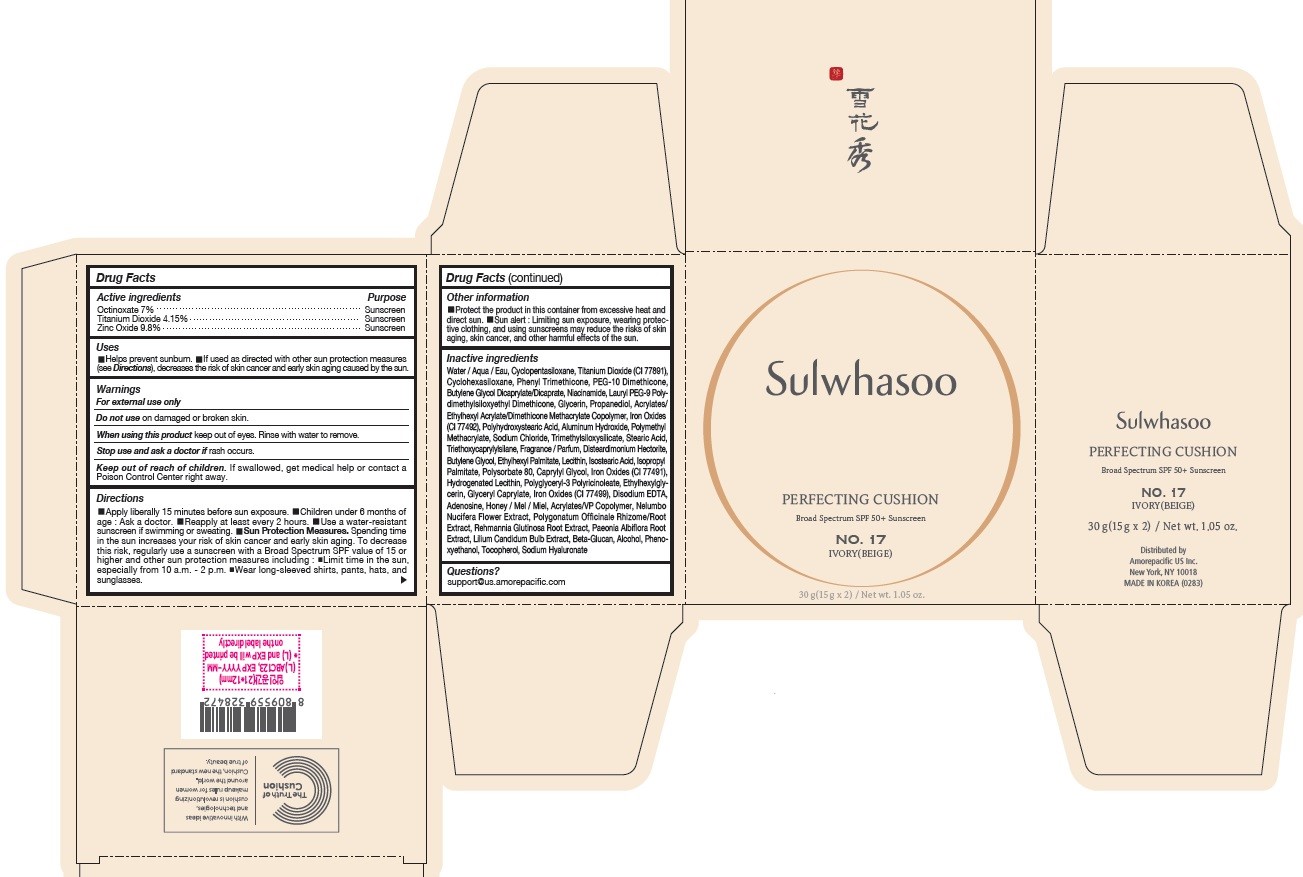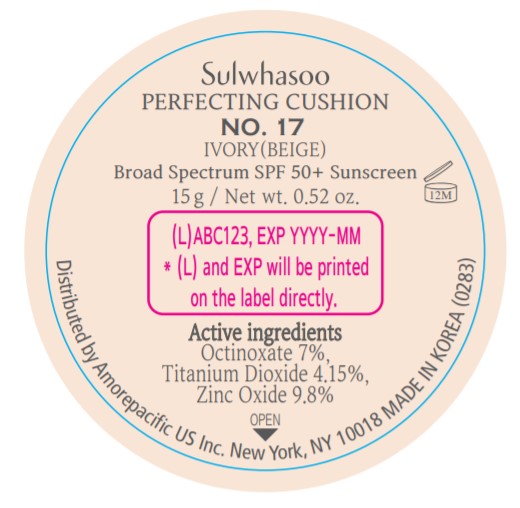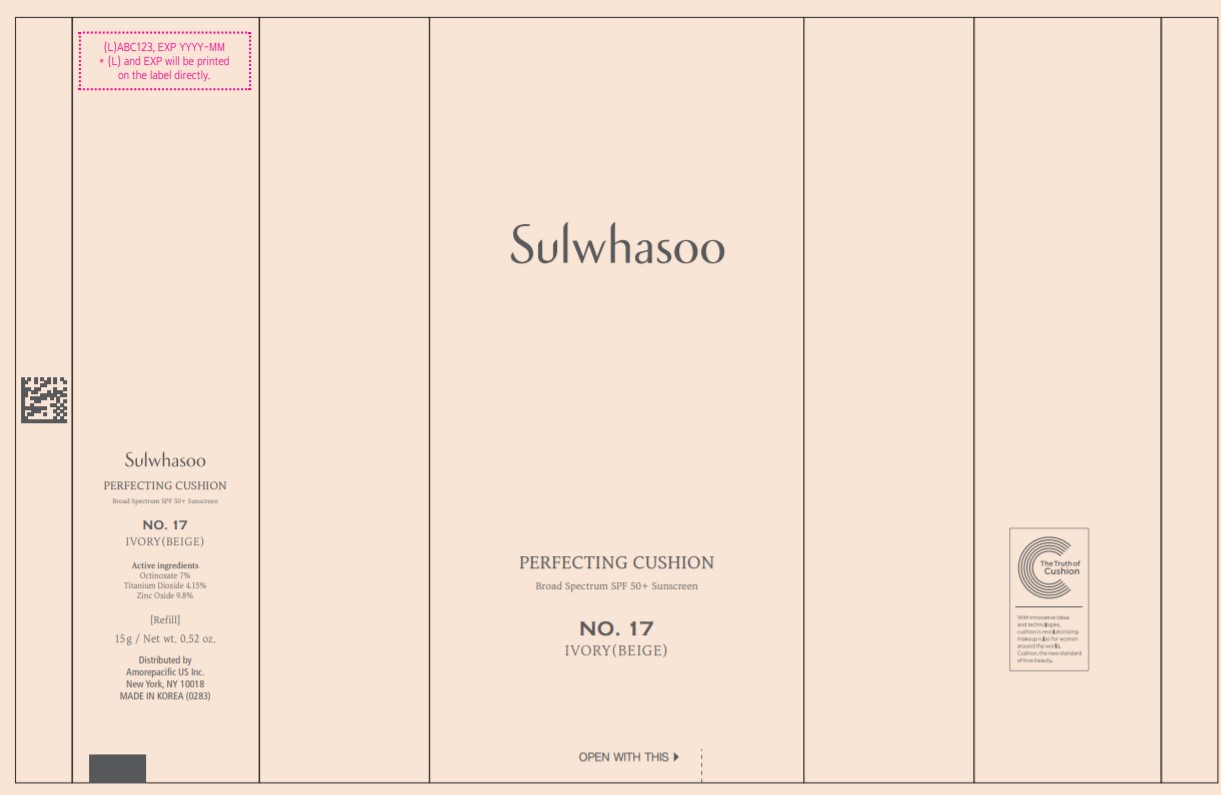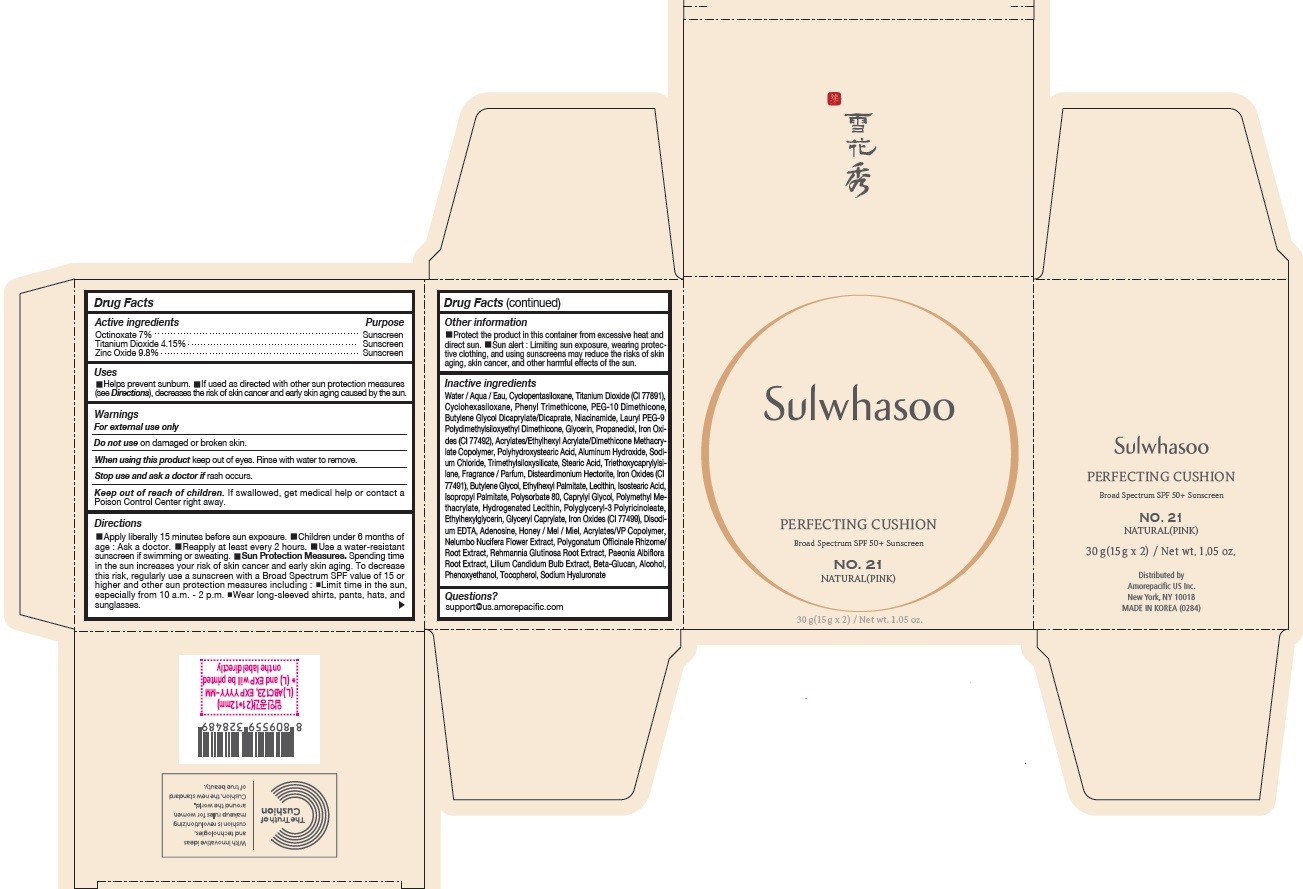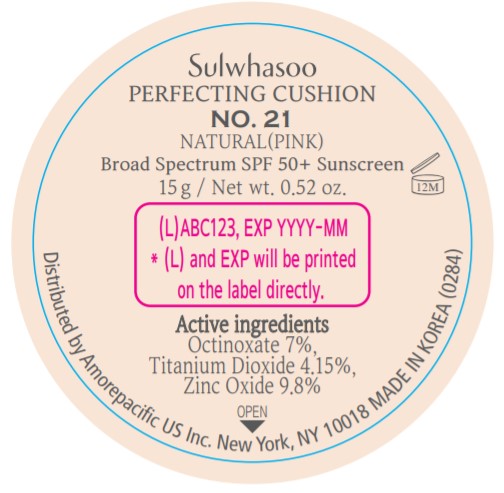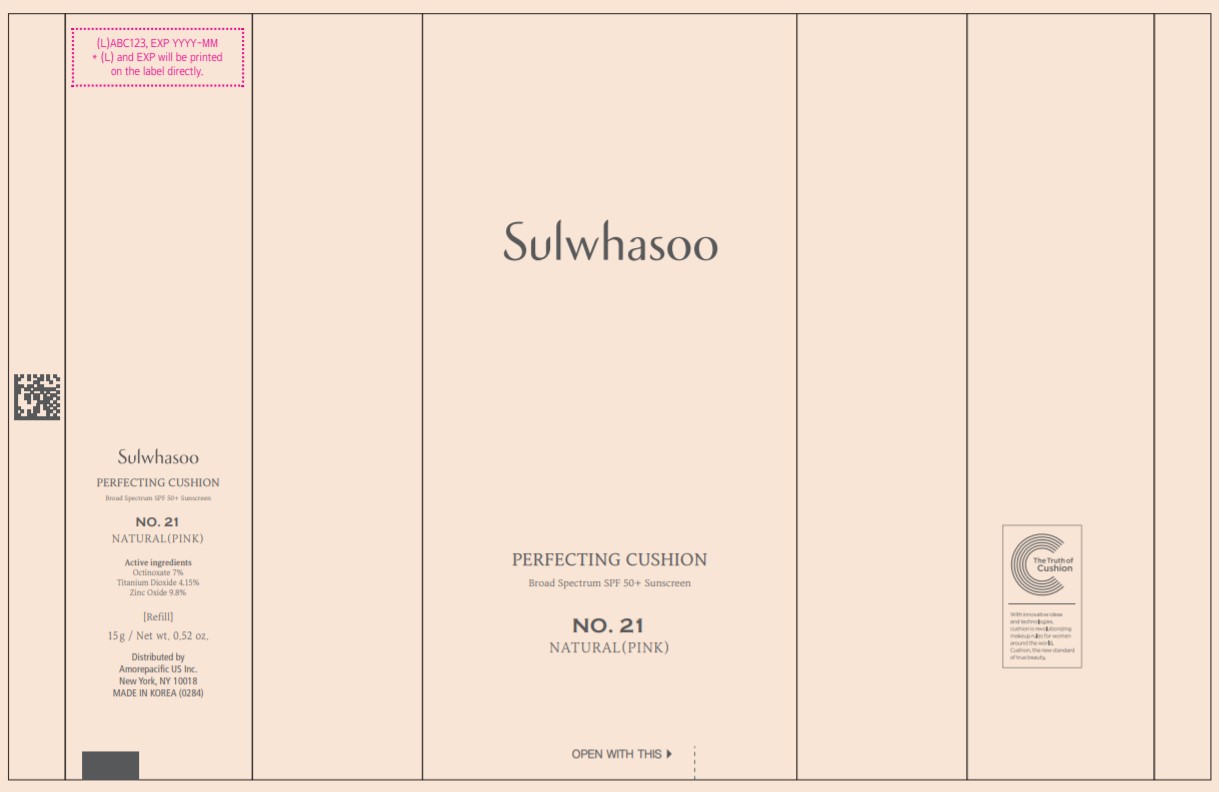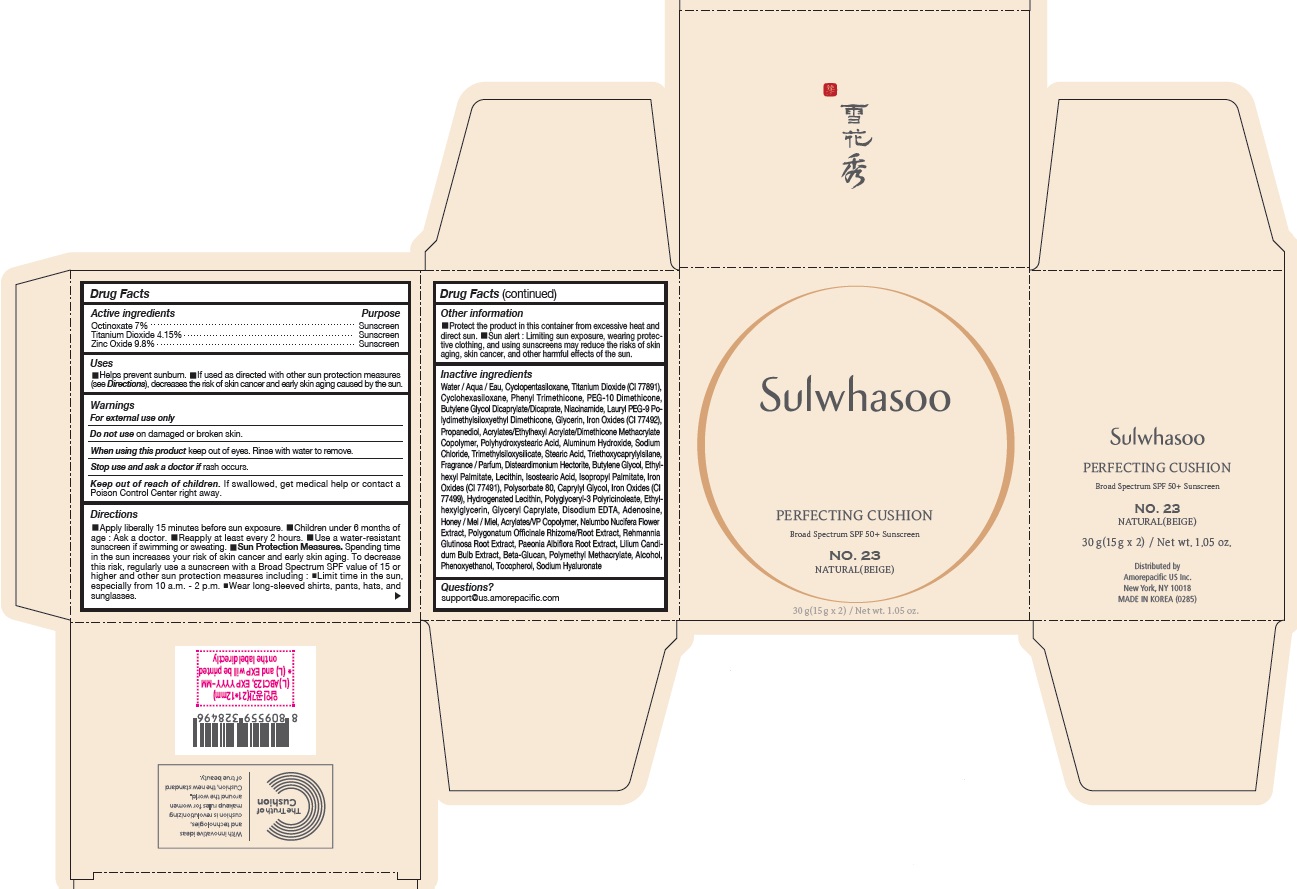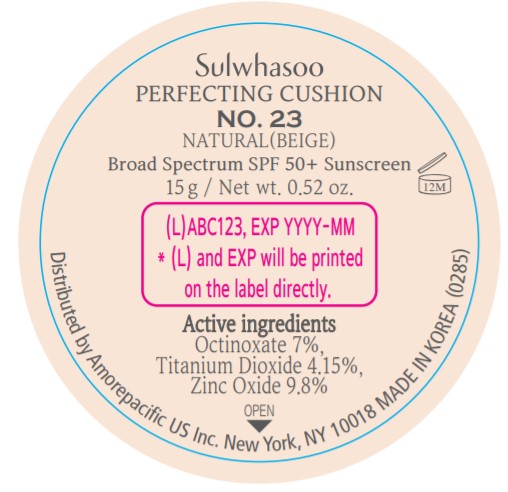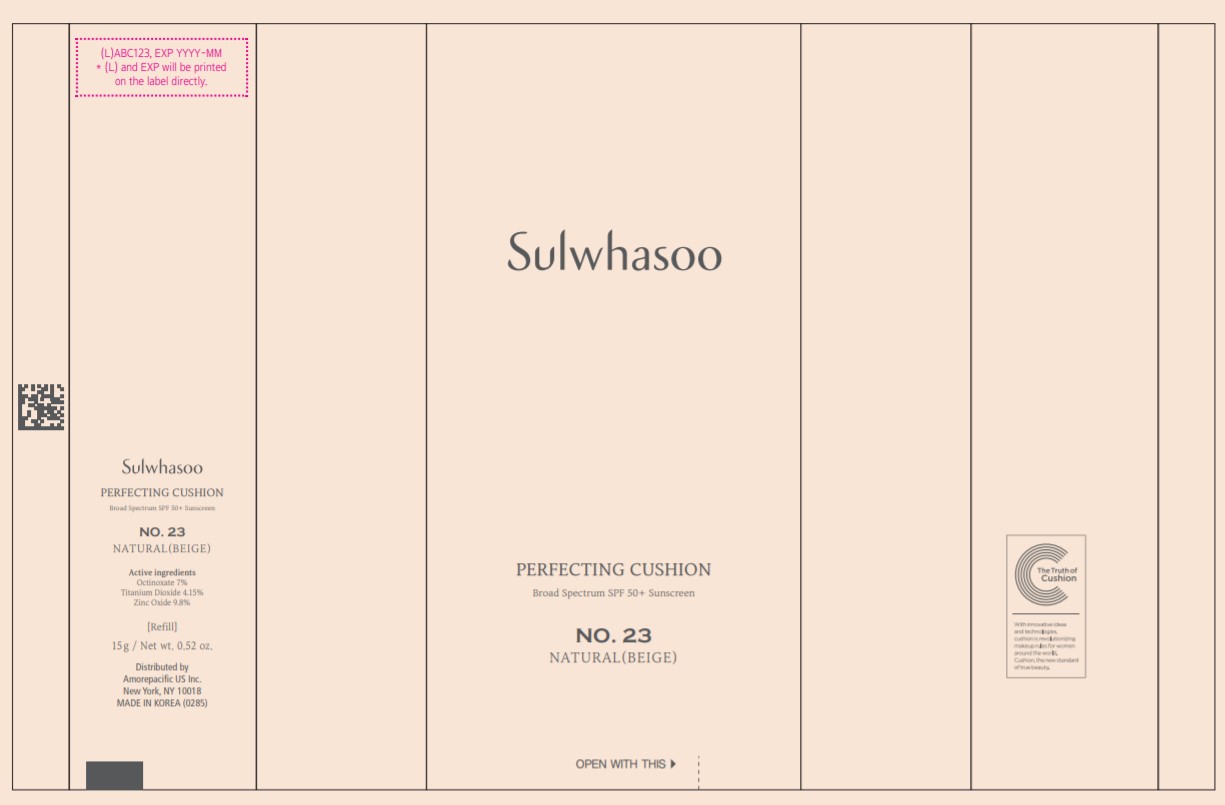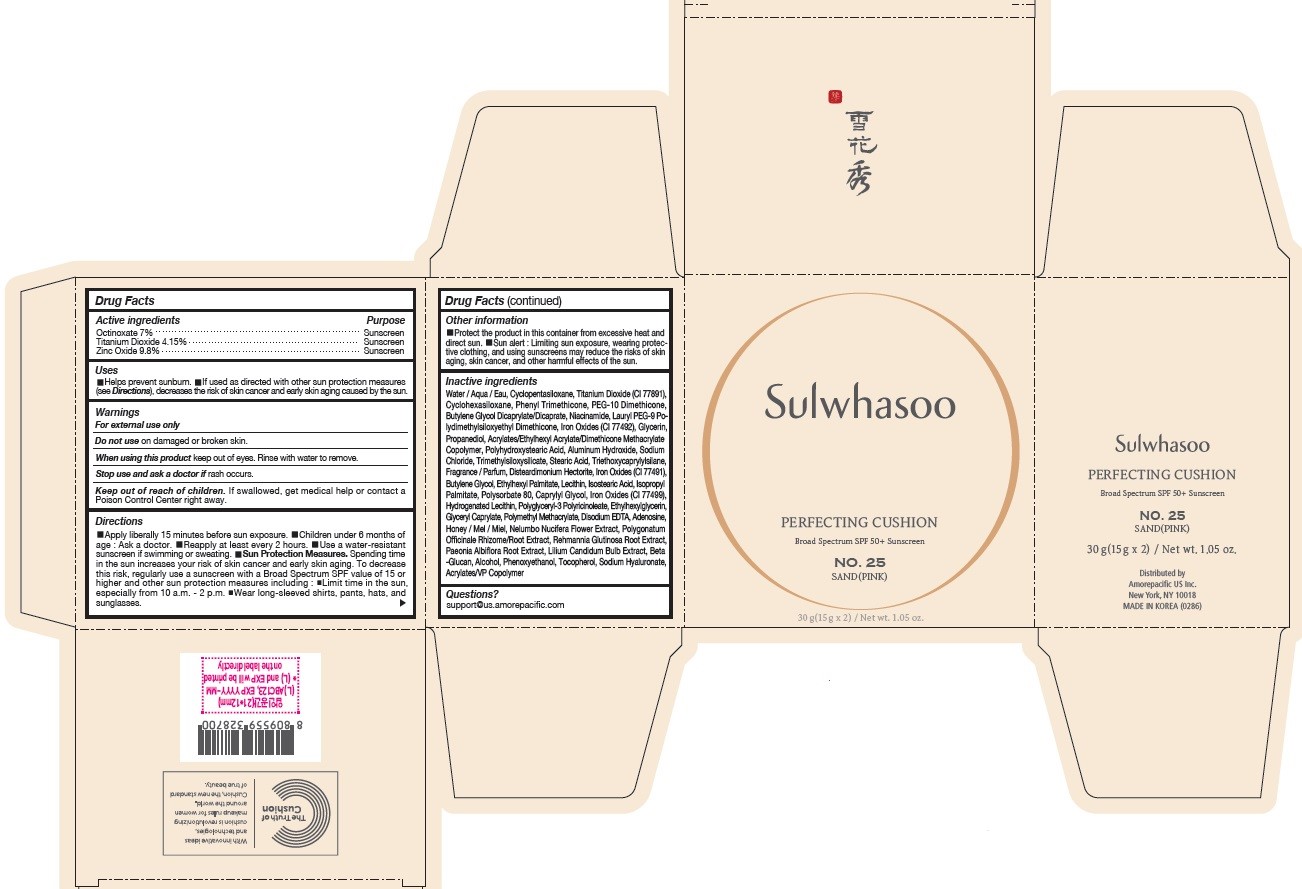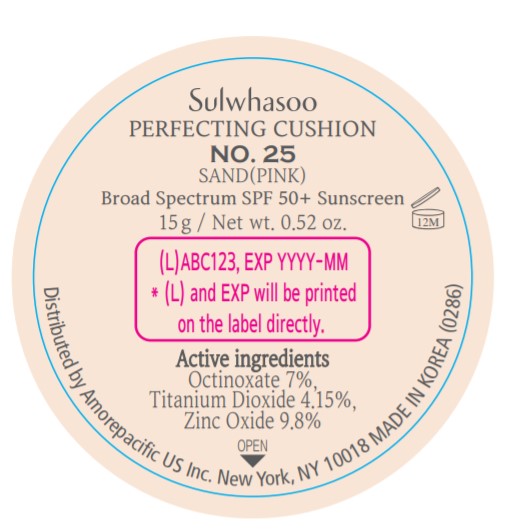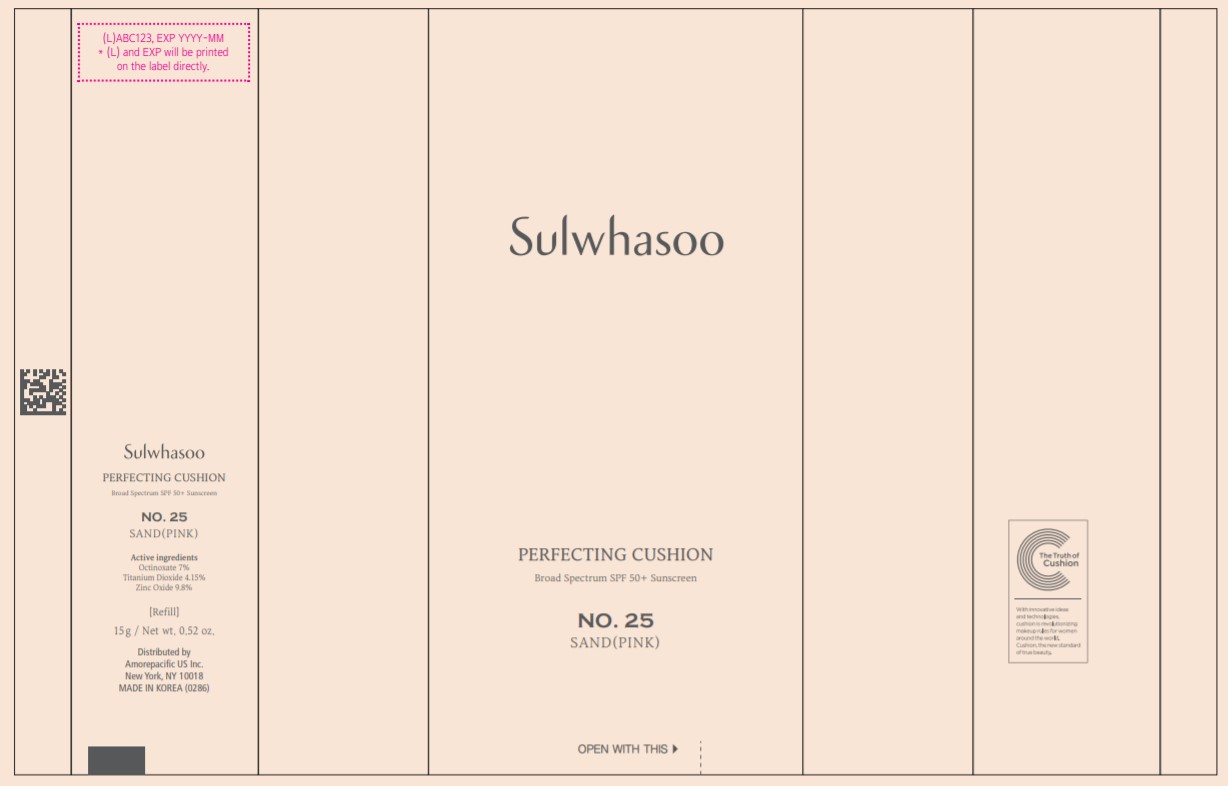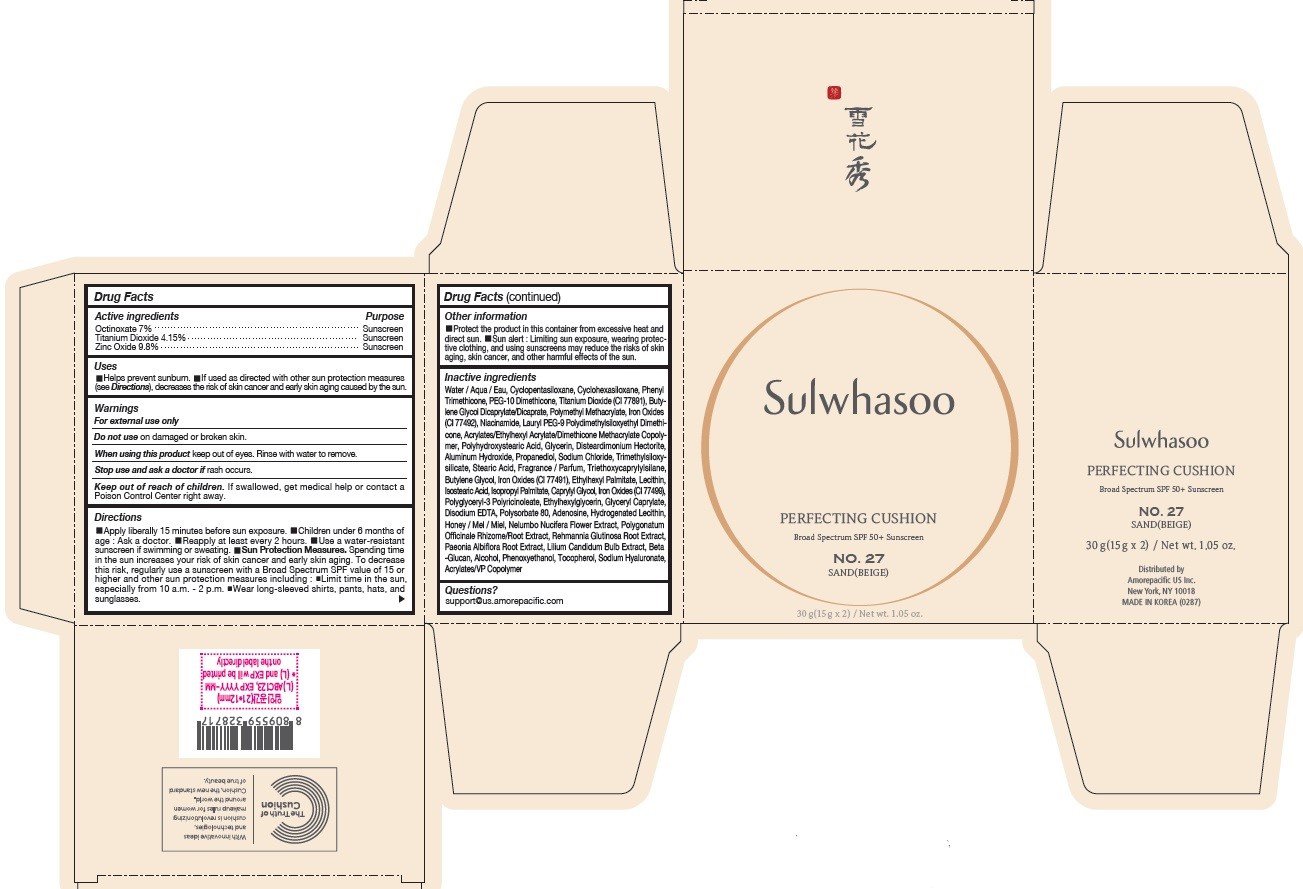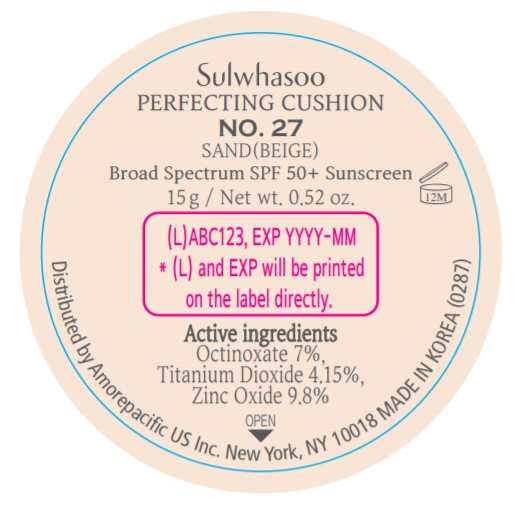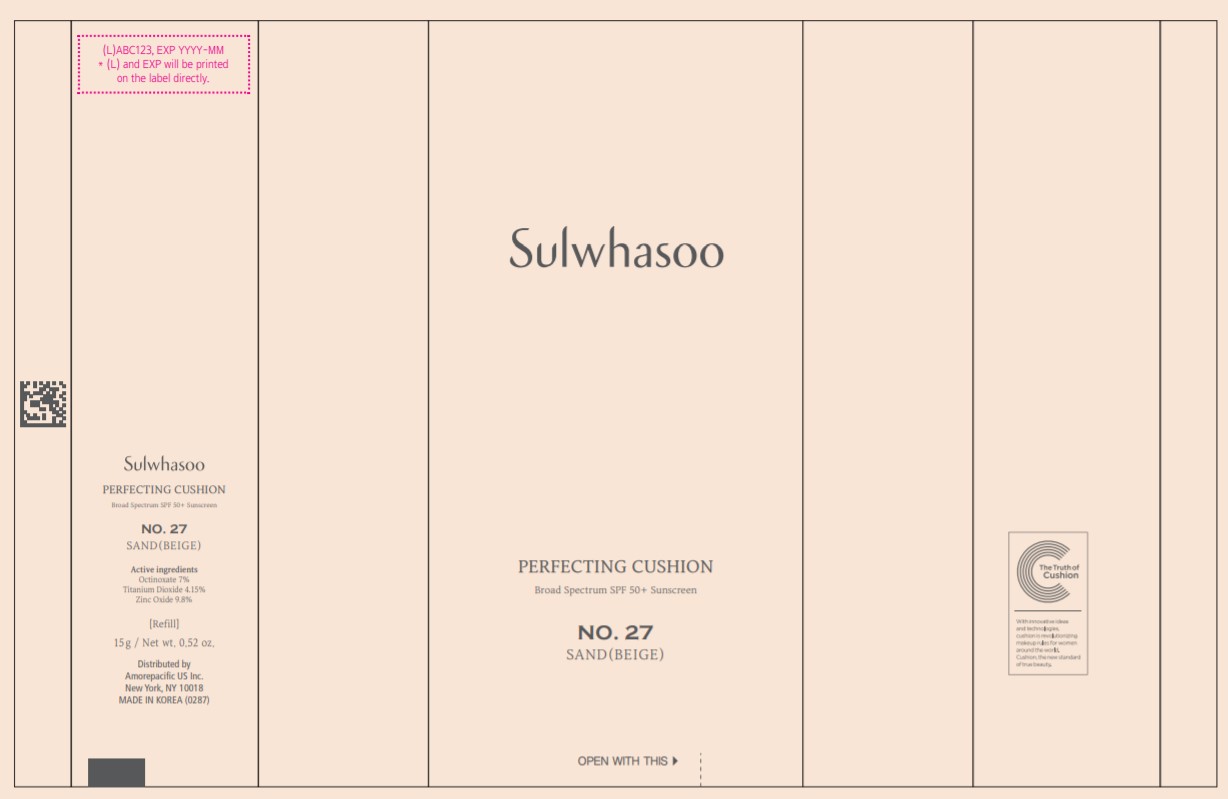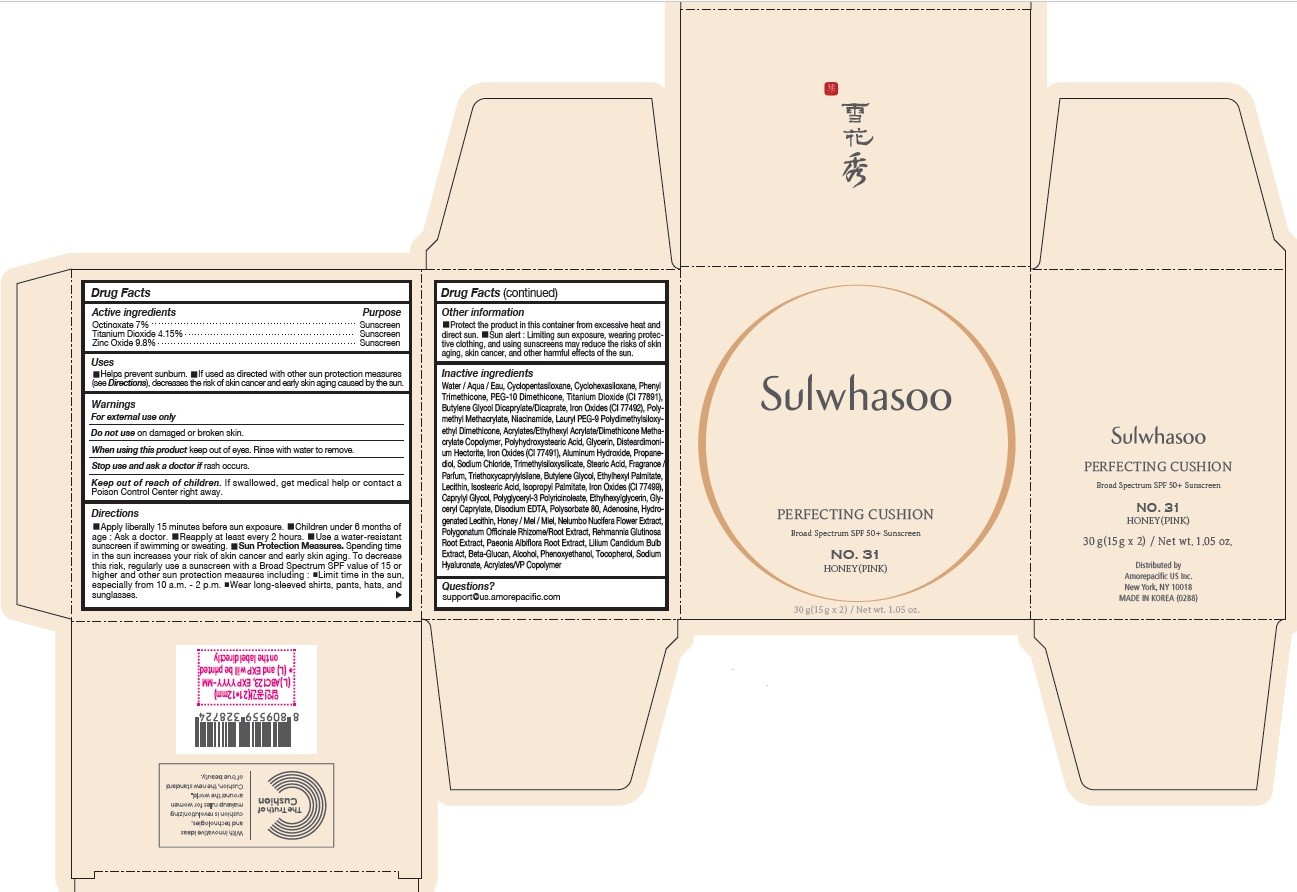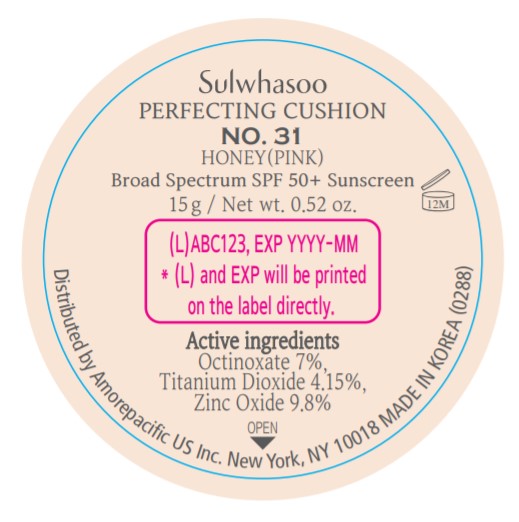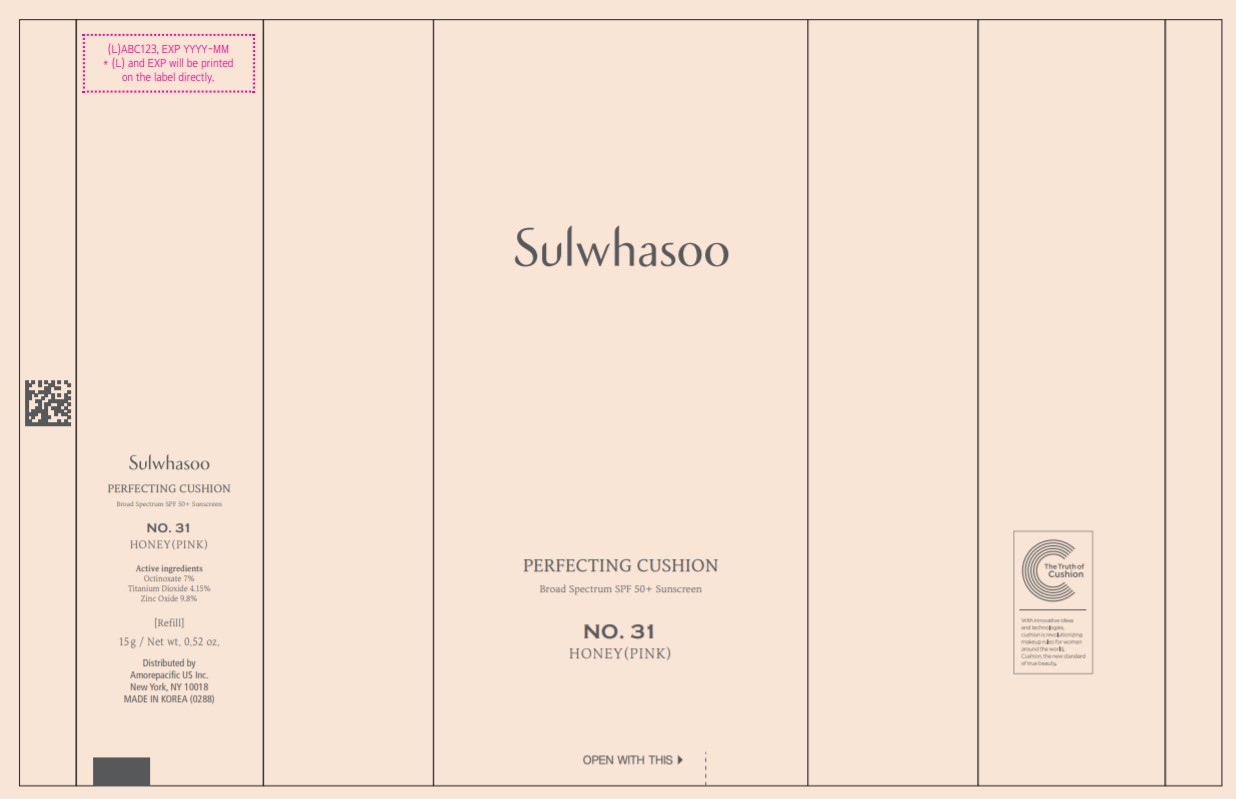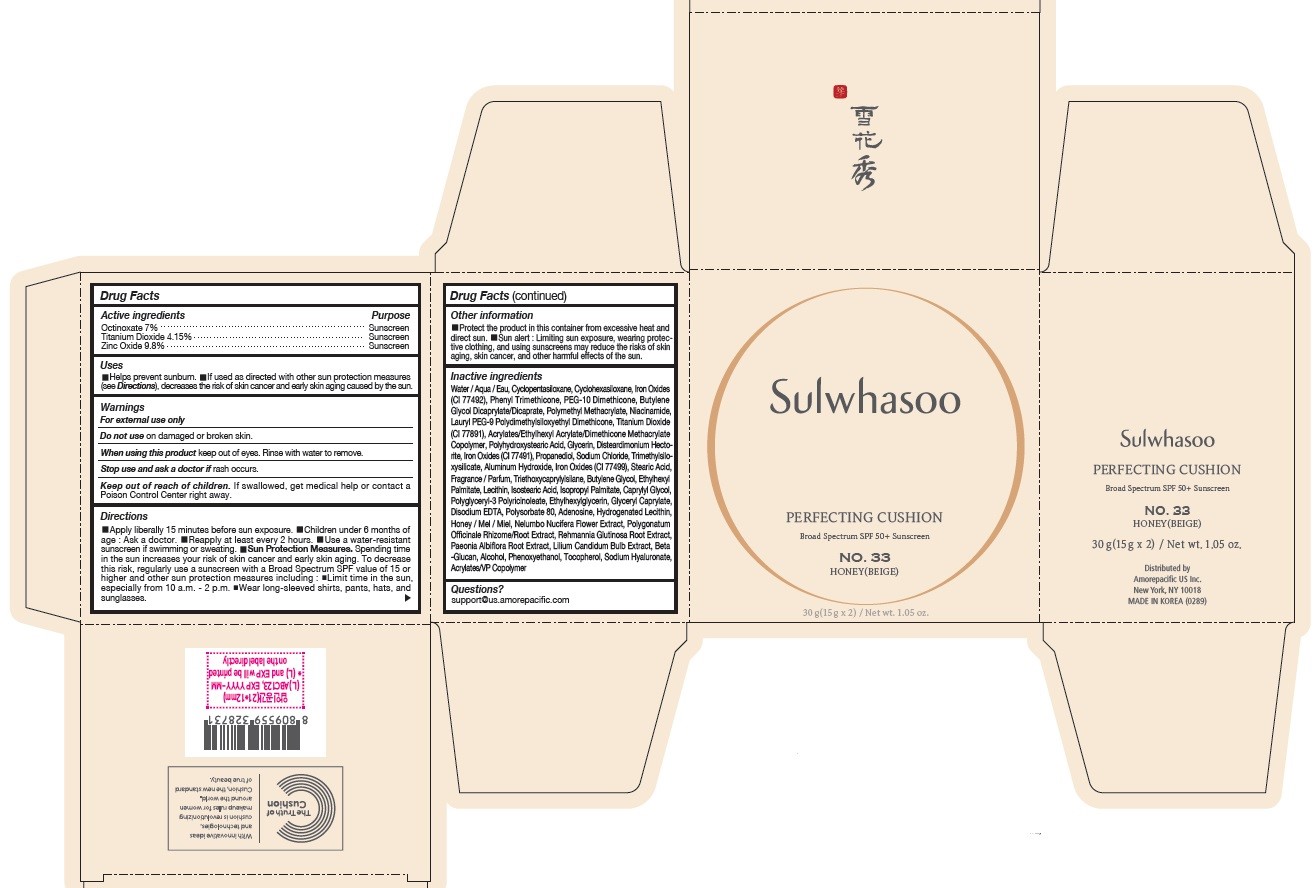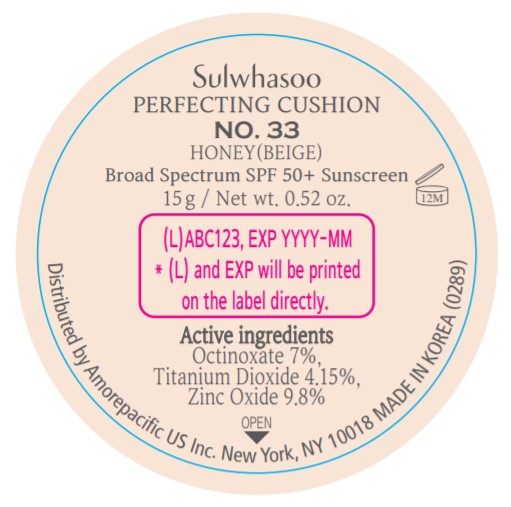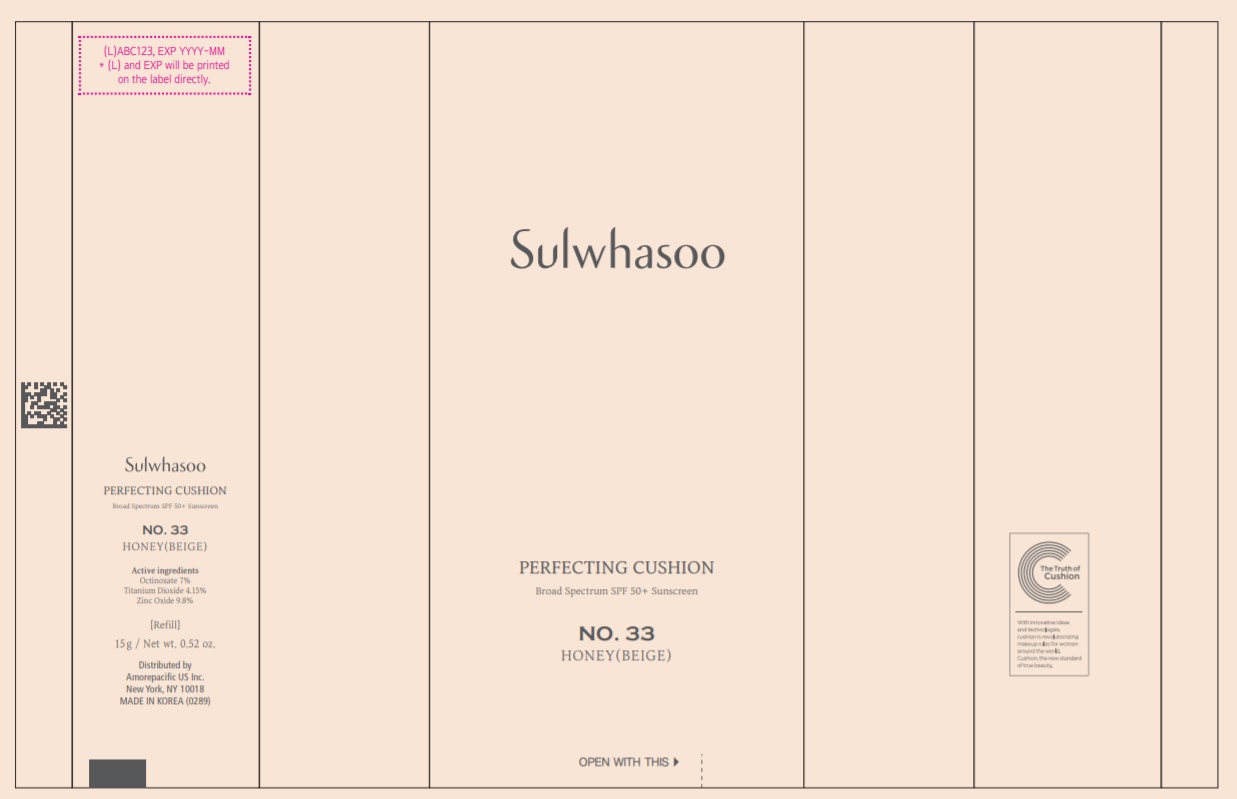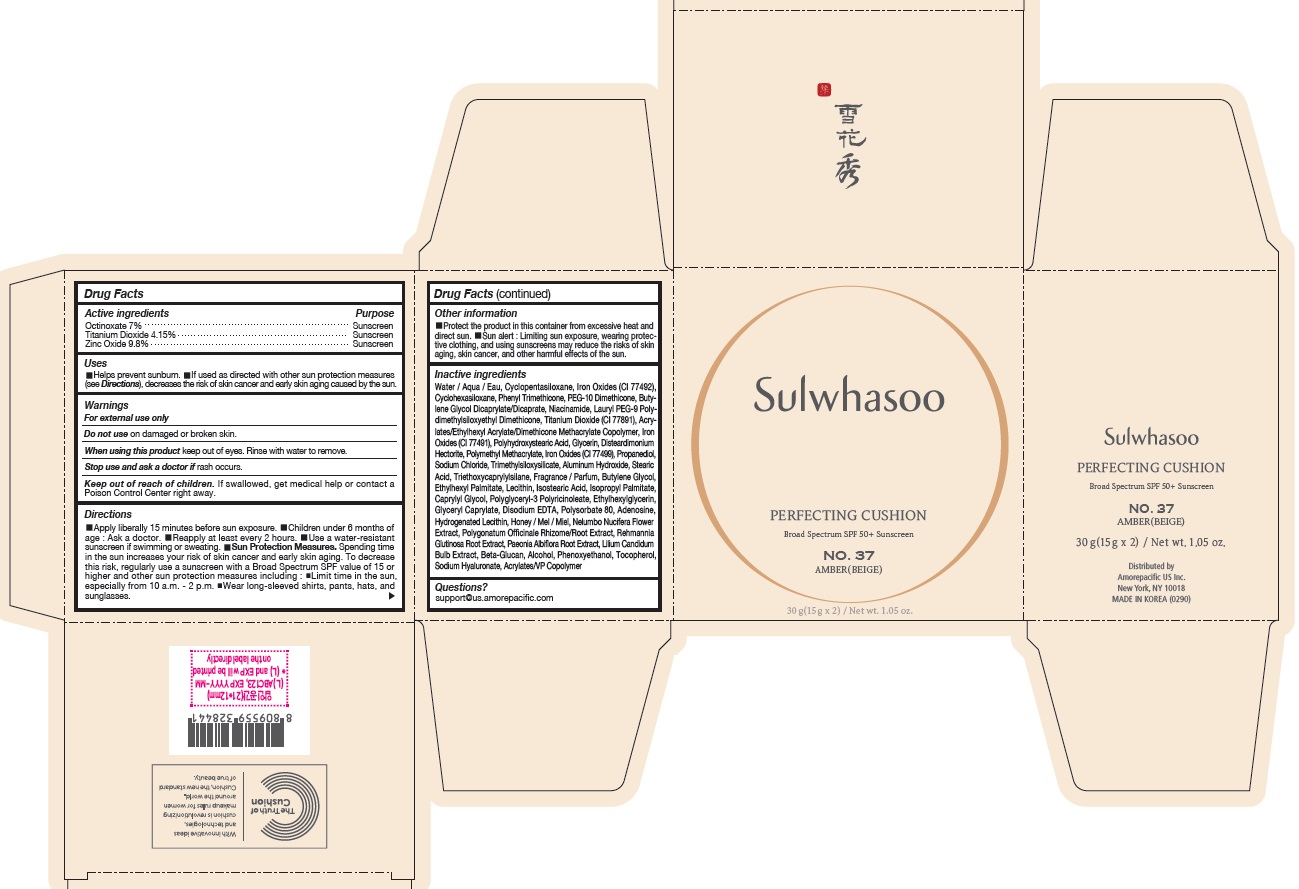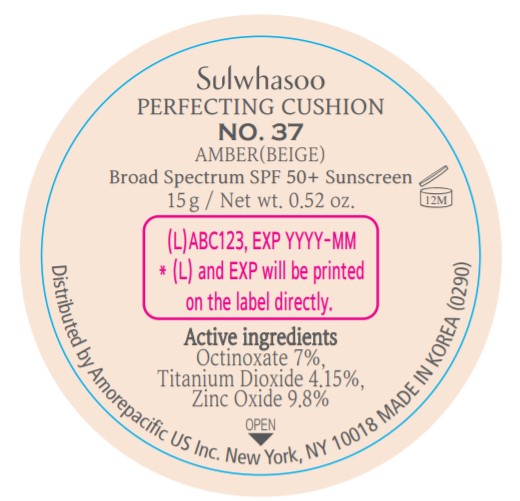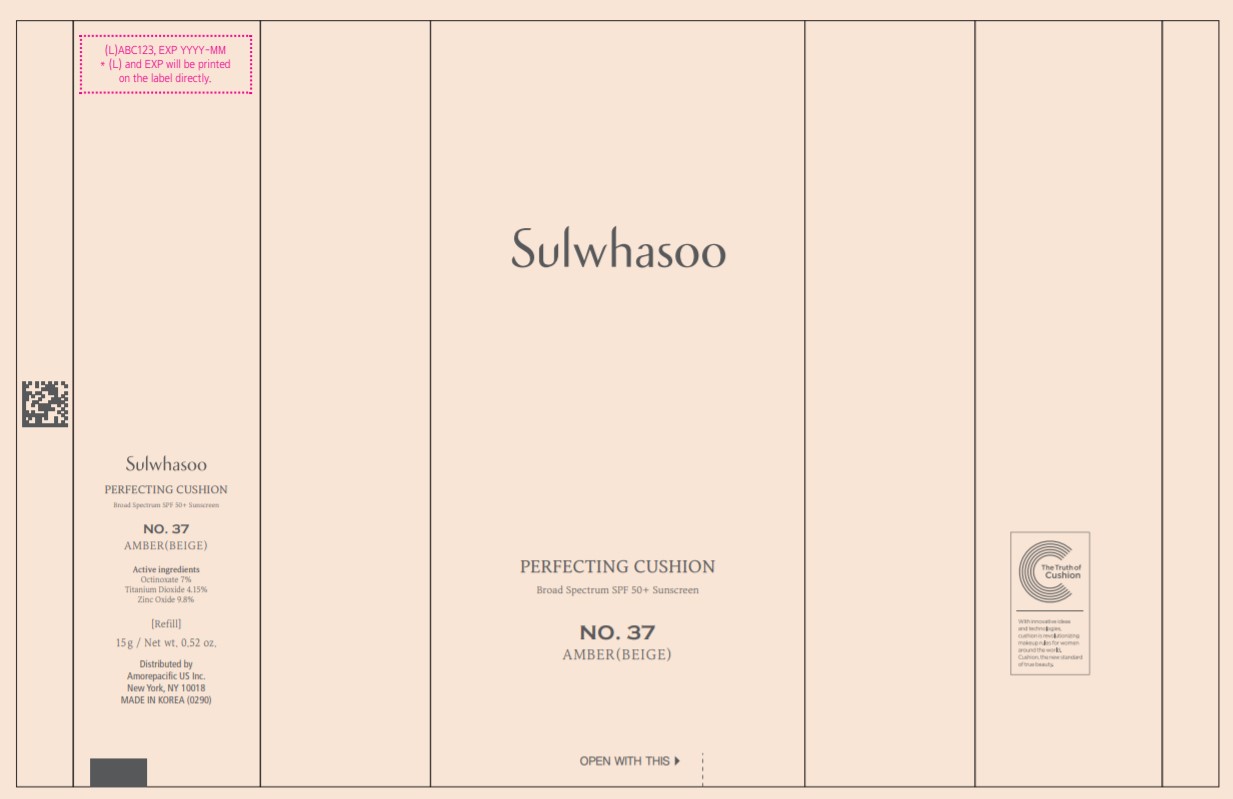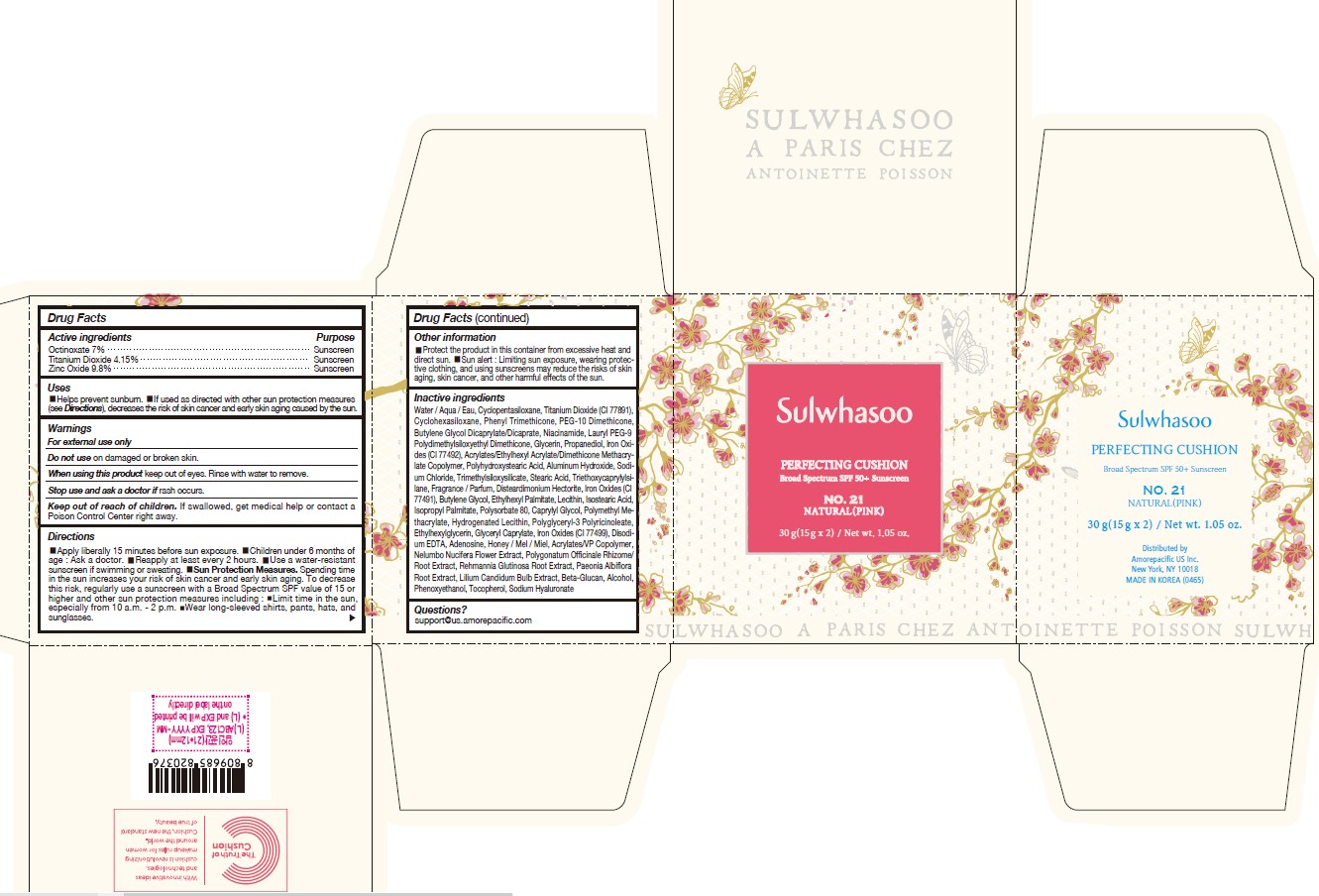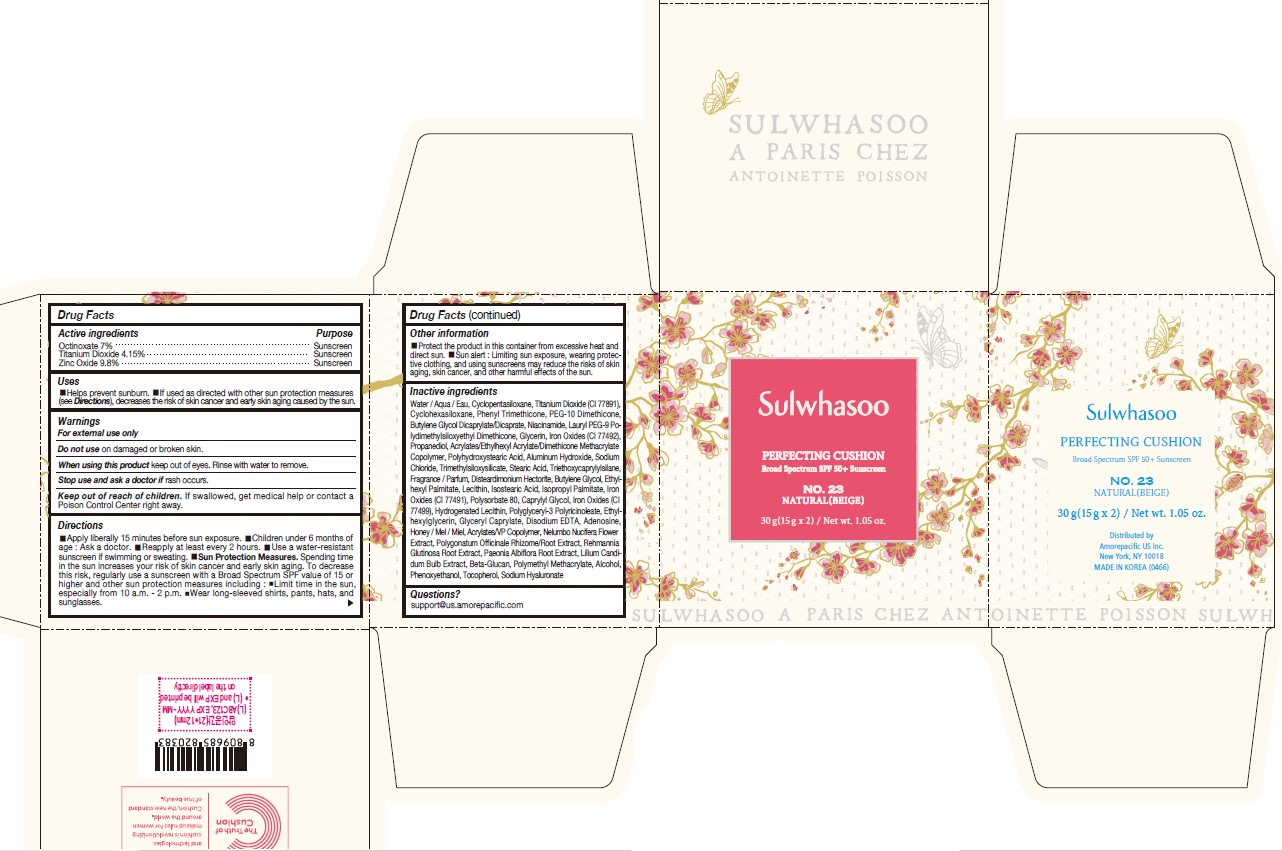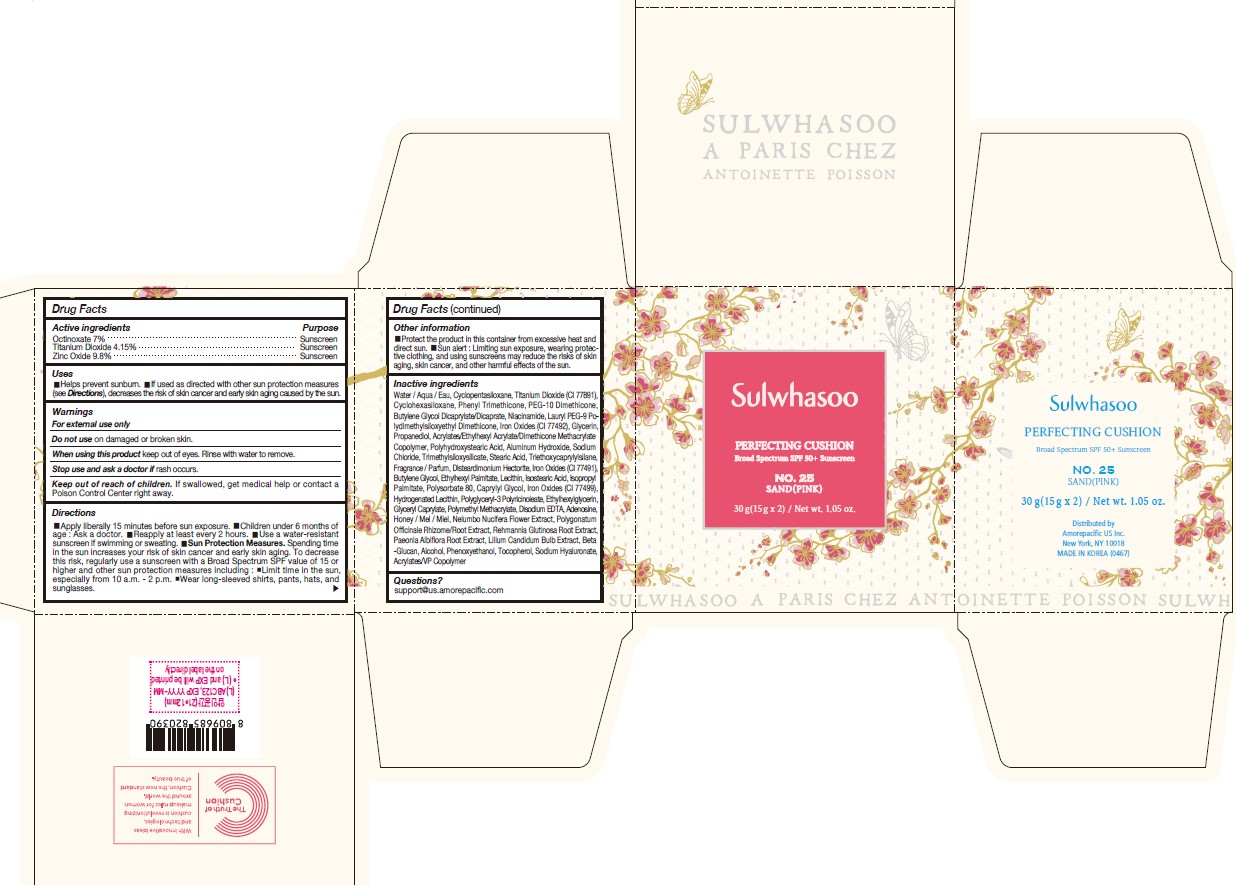 DRUG LABEL: SULWHASOO PERFECTING CUSHION NO. 21
NDC: 43419-077 | Form: LOTION
Manufacturer: Amorepacific Corporation
Category: otc | Type: HUMAN OTC DRUG LABEL
Date: 20251120

ACTIVE INGREDIENTS: OCTINOXATE 2.1 g/30 g; TITANIUM DIOXIDE 1.245 g/30 g; ZINC OXIDE 2.94 g/30 g
INACTIVE INGREDIENTS: HYALURONATE SODIUM; TOCOPHEROL; PHENOXYETHANOL; WATER; CYCLOMETHICONE 5; CYCLOMETHICONE 6; PHENYL TRIMETHICONE; PEG-10 DIMETHICONE (600 CST); BUTYLENE GLYCOL DICAPRYLATE/DICAPRATE; NIACINAMIDE; LAURYL PEG-9 POLYDIMETHYLSILOXYETHYL DIMETHICONE; GLYCERIN; PROPANEDIOL; POLY(METHYL METHACRYLATE; 450000 MW); POLYHYDROXYSTEARIC ACID (2300 MW); FERRIC OXIDE YELLOW; ALUMINUM HYDROXIDE; SODIUM CHLORIDE; TRIMETHYLSILOXYSILICATE (M/Q 1.0-1.2); STEARIC ACID; TRIETHOXYCAPRYLYLSILANE; DISTEARDIMONIUM HECTORITE; HYDROGENATED SOYBEAN LECITHIN; BUTYLENE GLYCOL; ETHYLHEXYL PALMITATE; ISOSTEARIC ACID; ISOPROPYL PALMITATE; POLYSORBATE 80; CAPRYLYL GLYCOL; FERRIC OXIDE RED; LECITHIN, SOYBEAN; ETHYLHEXYLGLYCERIN; GLYCERYL CAPRYLATE; FERROSOFERRIC OXIDE; EDETATE DISODIUM; ADENOSINE; HONEY; NELUMBO NUCIFERA FLOWER; POLYGONATUM ODORATUM ROOT; LILIUM CANDIDUM BULB; .BETA.-D-GLUCOPYRANOSE; ALCOHOL

SULWHASOO PERFECTING CUSHION

Drug Facts

ACTIVE INGREDIENTS W/W

OCTINOXATE 7%

TITANIUM DIOXIDE 4.15%

ZINC OXIDE 9.8%

PURPOSE

Sunscreen

USES

- Helps prevent sunburn
- If used as directed with other sun protection measures (see Directions), decreases the risk of skin cancer and early skin aging caused by the sun

WARNINGS

- For external use only

- Do not use on broken skin.

- When using this product avoid contact with eyes. If contact occurs, rinse thoroughly with water.

- Stop use and ask a doctor if rash occurs.

- Keep out of reach of children. If swallowed, call a poison control centre or get medical help right away.

DIRECTIONS

- Apply liberally 15 minutes before sun exposure
- Children under 6 months of age : Ask a doctor.
- Reapply at least every 2 hours.
- Use a water-resistant sunscreen if swimming or sweating.
- Sun Protection Measures. Spending time in the sun increases your risk of skin cancer and early skin aging. To decrease this risk, regularly use a sunscreen with a Broad Spectrum SPF value of 15 or higher and other sun protection measures including :
  - Limit time in the sun, especially from 10 a.m. - 2 p.m.
- Wear long-sleeved shirts, pants, hats, and sunglasses.

INACTIVE INGREDIENTS

Water / Aqua / Eau, Cyclopentasiloxane, Titanium Dioxide (CI 77891), Cyclohexasiloxane, Phenyl Trimethicone, PEG-10 Dimethicone, Butylene Glycol Dicaprylate/Dicaprate, Niacinamide, Lauryl PEG-9 Polydimethylsiloxyethyl Dimethicone, Glycerin, Propanediol, Acrylates/Ethylhexyl Acrylate/Dimethicone Methacrylate Copolymer, Polymethyl Methacrylate, Polyhydroxystearic Acid, Iron Oxides (CI 77492), Aluminum Hydroxide, Sodium Chloride, Trimethylsiloxysilicate, Stearic Acid, Triethoxycaprylylsilane, Fragrance / Parfum, Disteardimonium Hectorite, Butylene Glycol, Ethylhexyl Palmitate, Lecithin, Isostearic Acid, Isopropyl Palmitate, Polysorbate 80, Caprylyl Glycol, Iron Oxides (CI 77491), Hydrogenated Lecithin, Polyglyceryl-3 Polyricinoleate, Ethylhexylglycerin, Glyceryl Caprylate, Iron Oxides (CI 77499), Disodium EDTA, Adenosine, Honey / Mel / Miel, Acrylates/VP Copolymer, Nelumbo Nucifera Flower Extract, Polygonatum Officinale Rhizome/Root Extract, Rehmannia Glutinosa Root Extract, Paeonia Albiflora Root Extract, Lilium Candidum Bulb Extract, Beta-Glucan, Alcohol, Phenoxyethanol, Tocopherol, Sodium Hyaluronate

OTHER INFORMATION

- Protect the product in this container from excessive heat and direct sun.
- Sun alert : Limiting sun exposure, wearing protective clothing, and using sunscreens may reduce the risks of skin aging, skin cancer, and other harmful effects of the sun.

PRINCIPAL DISPLAY PANEL - NO. 11 PORCELAIN(PINK)

Sulwhasoo

PERFECTING CUSHION
BROAD SPECTRUM 50+ SUNSCREEN

NO. 11
PORCELAIN(PINK)

30 g(15 g x 2) / Net wt. 1.05 oz.

PRINCIPAL DISPLAY PANEL - NO. 15 IVORY(PINK)

Sulwhasoo

PERFECTING CUSHION
BROAD SPECTRUM 50+ SUNSCREEN

NO. 15
IVORY(PINK)

30 g(15 g x 2) / Net wt. 1.05 oz.

PRINCIPAL DISPLAY PANEL - NO. 17 IVORY(BEIGE)

Sulwhasoo

PERFECTING CUSHION
BROAD SPECTRUM SPF50+ SUNSCREEN

NO. 17

IVORY(BEIGE)

30 g(15 g x 2) / Net wt. 1.05 oz.

PRINCIPAL DISPLAY PANEL - NO. 21 NATURAL(PINK)

Sulwhasoo

PERFECTING CUSHION
BROAD SPECTRUM 50+ SUNSCREEN

NO. 21

NATURAL(PINK)

30 g(15 g x 2) / Net wt. 1.05 oz.

Sulwhasoo Perfecting Cushion No. 21 Natural (Pink) Spring Limited Edition

Sulwhasoo

Perfecting Cushion

Broad Spectrum SPF 50+ Sunscreen

NO. 21

Natural (Pink)

30g (15g x 2) / Net wt. 1.05 oz.

PRINCIPAL DISPLAY PANEL - NO. 23 NATURAL(BEIGE)

Sulwhasoo

PERFECTING CUSHION
BROAD SPECTRUM 50+ SUNSCREEN

NO. 23
NATURAL(BEIGE)
30 g(15 g x 2) / Net wt. 1.05 oz.

Sulwhasoo Perfecting Cushion No. 23 Natural (Beige) Spring Limited Edition

Sulwhasoo

Perfecting Cushion

Broad Spectrum SPF 50+ Sunscreen

NO. 23

Natural (Beige)

30g (15g x 2) / Net wt. 1.05 oz.

PRINCIPAL DISPLAY PANEL - NO. 25 SAND(PINK)

Sulwhasoo

PERFECTING CUSHION
BROAD SPECTRUM SPF50+ SUNSCREEN

NO. 25

SAND(PINK)

30 g(15 g x 2) / Net wt. 1.05 oz.

Sulwhasoo Perfecting Cushion No. 25 Sand (Pink) Spring Limited Edition

Sulwhasoo

Perfecting Cushion

Broad Spectrum SPF 50+ Sunscreen

NO. 25

Sand (Pink)

30g (15g x 2) / Net wt. 1.05 oz.

PRINCIPAL DISPLAY PANEL - NO. 27 SAND(BEIGE)

Sulwhasoo

PERFECTING CUSHION
BROAD SPECTRUM 50+ SUNSCREEN

NO. 27

SAND(BEIGE)
30 g(15 g x 2) / Net wt. 1.05 oz.

PRINCIPAL DISPLAY PANEL - NO. 31 HONEY(PINK)

Sulwhasoo

PERFECTING CUSHION
BROAD SPECTRUM 50+ SUNSCREEN

NO. 31
HONEY(PINK)

30 g(15 g x 2) / Net wt. 1.05 oz.

PRINCIPAL DISPLAY PANEL - NO. 33 HONEY(BEIGE)

Sulwhasoo

PERFECTING CUSHION
BROAD SPECTRUM 50+ SUNSCREEN

NO. 33

HONEY(BEIGE)

30 g(15 g x 2) / Net wt. 1.05 oz.

PRINCIPAL DISPLAY PANEL - NO. 37 AMBER(BEIGE)

Sulwhasoo

PERFECTING CUSHION
BROAD SPECTRUM 50+ SUNSCREEN

NO. 37
AMBER(BEIGE)

30 g(15 g x 2) / Net wt. 1.05 oz.